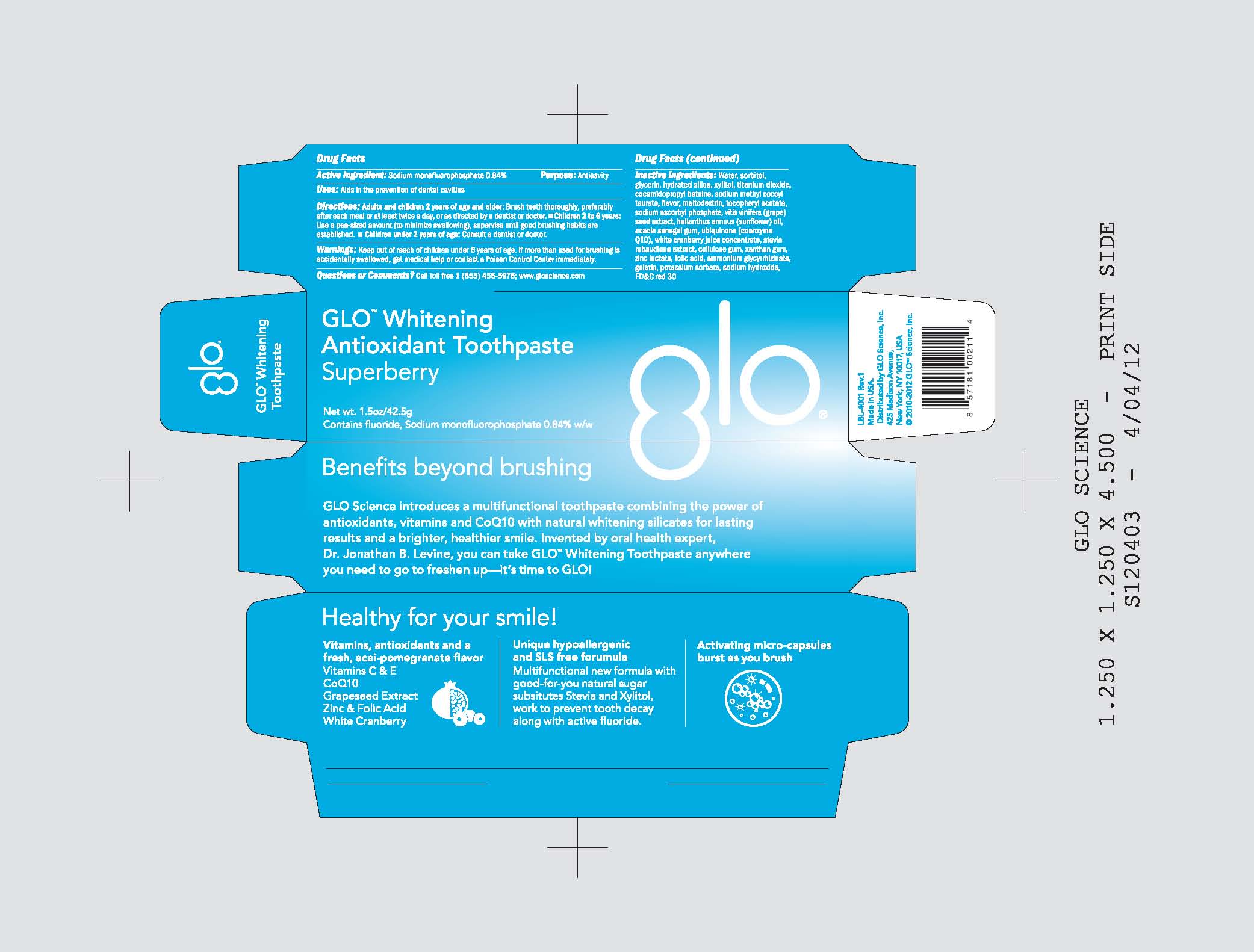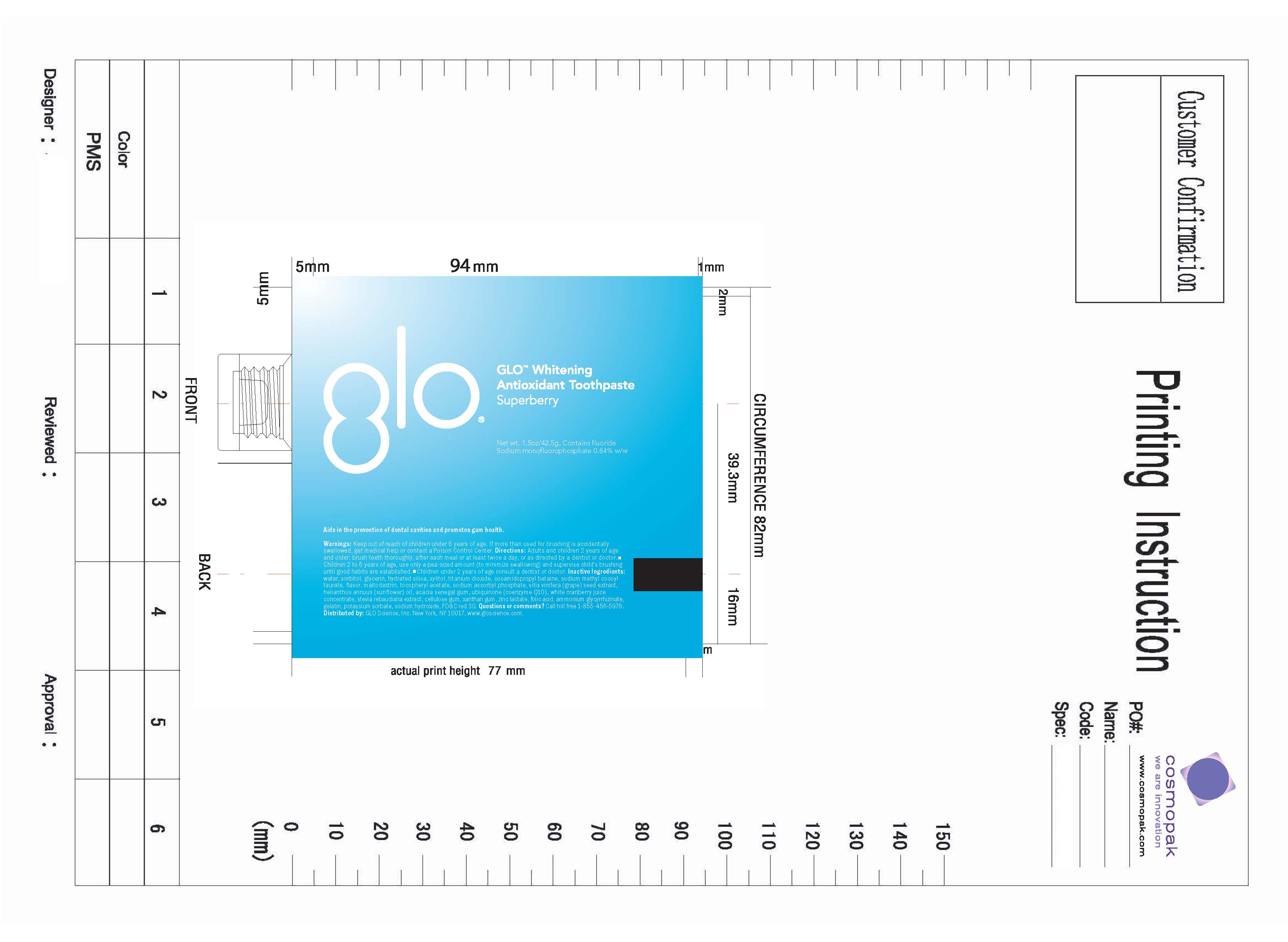 DRUG LABEL: Glo Science
NDC: 49993-861 | Form: PASTE, DENTIFRICE
Manufacturer: GLO Science Inc
Category: otc | Type: HUMAN OTC DRUG LABEL
Date: 20120514

ACTIVE INGREDIENTS: SODIUM MONOFLUOROPHOSPHATE 0.84 g/100 g
INACTIVE INGREDIENTS: SORBITOL; WATER; POTASSIUM SORBATE; .ALPHA.-TOCOPHEROL ACETATE; ZINC LACTATE; FOLIC ACID; CRANBERRY; VITIS VINIFERA SEED; UBIDECARENONE; SODIUM ASCORBYL PHOSPHATE; STEVIA REBAUDIUNA LEAF; COCAMIDOPROPYL BETAINE; AMMONIUM GLYCYRRHIZATE; TITANIUM DIOXIDE; SODIUM HYDROXIDE; GLYCERIN; CARBOXYMETHYLCELLULOSE SODIUM  ; HYDRATED SILICA; SODIUM METHYL COCOYL TAURATE; SUNFLOWER OIL; GELATIN; ACACIA; XANTHAN GUM

Drug Facts

Active ingredients

Active Ingredient: SODIUM MONOFLUOROPHOSPHATE 0.84% FLUORIDE ION PURPOSE: ANTICAVITY

Use

- aids in the prevention of dental cavities

Uses

aids in the prevention of dental cavities

Keep out of reach of children under 6 years of age

Directions

Adults and children 2 years of age and older: Brush teeth thoroughly, preferably
after each meal or at least twice a day or as recommended by a dentist or doctor.
Children 2 to 6 years: Use a pea sized amount (to minimize swallowing), supervise until good
brushing habits are established. Children under 2 years of age:Consult a dentist or doctor.

Inactive ingredients

Water, sorbitol, glycerin, hydrated silica, xylitol, titanium dioxide, Cocamidopropyl Betaine, Sodium Methyl Cocoyl Taurate, Flavor, Maltodextrin, Tocopheryl Acetate, Sodium Ascorbyl Phosphate, Vitis Vinifera (Grape) Seed Extract, Helianthus Annuus (Sunflower) Oil, Acacia Senegal Gum, Ubiquinone (Coenzyme Q10), White Cranberry Juice Concentrate, Stevia Rebaudiana Extract, Cellulose Gum, Xanthan Gum, Zinc Lactate, Folic Acid, Ammonium Glycyrrhizinate, Gelatin, Potassium Sorbate, Sodium Hydroxide, FDC Red 30

Warnings

Keep out of reach of children under 6 years of age. If more than used for brushing

is accidentally swallowed, get medical help or contact a poison control center immediately.